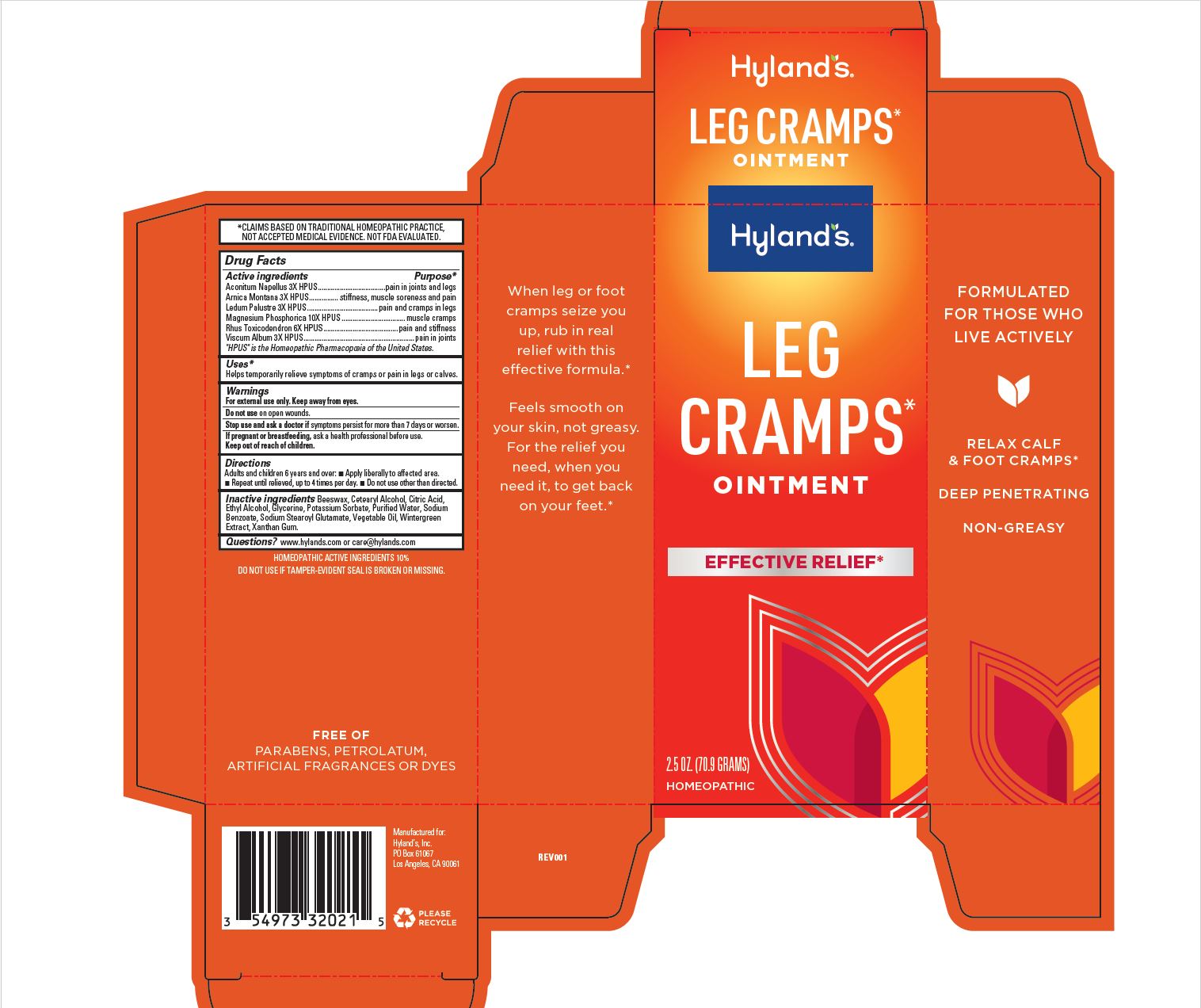 DRUG LABEL: Leg Cramps
NDC: 54973-3202 | Form: OINTMENT
Manufacturer: Hyland's Inc.
Category: homeopathic | Type: HUMAN OTC DRUG LABEL
Date: 20250114

ACTIVE INGREDIENTS: ACONITUM NAPELLUS 3 [hp_X]/1 g; ARNICA MONTANA 3 [hp_X]/1 g; LEDUM PALUSTRE TWIG 3 [hp_X]/1 g; MAGNESIUM PHOSPHATE, DIBASIC TRIHYDRATE 10 [hp_X]/1 g; TOXICODENDRON PUBESCENS LEAF 6 [hp_X]/1 g; VISCUM ALBUM FRUITING TOP 3 [hp_X]/1 g
INACTIVE INGREDIENTS: ALCOHOL; YELLOW WAX; CETOSTEARYL ALCOHOL; CITRIC ACID MONOHYDRATE; POTASSIUM SORBATE; WATER; SODIUM BENZOATE; SODIUM STEAROYL GLUTAMATE; GLYCERIN; CORN OIL; GAULTHERIA PROCUMBENS LEAF; XANTHAN GUM

Leg Cramps Ointment

Purpose

Temporarily relieves symptoms of cramps or pain in legs or calves.

Drug Facts

Active ingredients

Active ingredients | Purpose
Aconitum Napellus 3X HPUS | pain in joints and legs
Arnica Montana 3X HPUS | stiffness, muscle soreness and pain
Ledum Palustre 3X HPUS | pain and cramps in legs
Magnesium Phosphorica 10X HPUS | muscle cramps
Rhus Toxicodendron 6X HPUS | pain and stiffness
Viscum Album 3X HPUS | pain in joints

"HPUS" is the Homeopathic Pharmacopoeia of the United States.

Uses

Helps temporarily relieve the symptoms of cramps and pains in legs and calves.

Warnings

Do not use

on open wounds.

Stop use and ask a doctor if

symptoms persist for more than 7 days or worsen.

If pregnant or breastfeeding

ask a health professional before use.

Directions

Adults and children 6 years and over: ■ Apply liberally to affected area. ■ Repeat until relieved, up to 4 times per day. ■ Do not use other than directed.

Inactive ingredients

Beeswax, Cetearyl Alcohol, Citric Acid, Potassium Sorbate, Purified Water, Sodium Benzoate, Sodium Stearoyl Glutamate, Vegetable Glycerine, Vegetable Oil, Wintergreen Extract, Xanthan Gum.

Questions?

www.hylands.com or care@hylands.com

Dosage and Administration

Directions
Adults and children 6 years and over:  Apply liberally to affected area.
 Repeat until relieved, up to 4 times per day.  Do not use other than directed.

Indications and Usage

Uses

Helps temporarily relieve symptoms of cramps or pain in legs or calves.

PRINCIPAL DISPLAY PANEL

Hyland's

NATURALS™
LEG

CRAMPS

OINTMENT

EFFECTIVE RELIEF*

HOMEOPATHIC

2.5 OZ. (70.9 GRAMS)